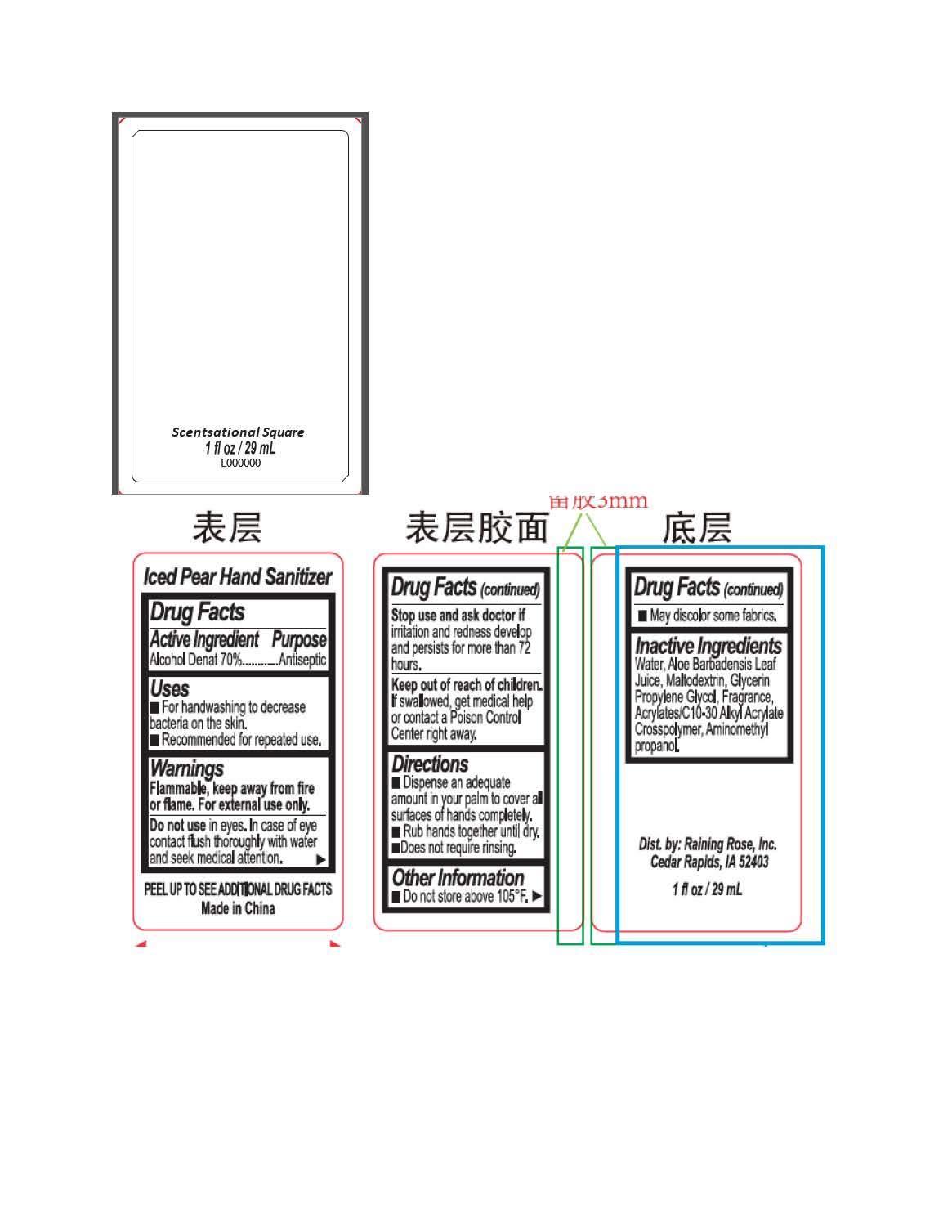 DRUG LABEL: Scentsational Square Hand Sanitizer
NDC: 65692-2081 | Form: GEL
Manufacturer: Raining Rose, Inc
Category: otc | Type: HUMAN OTC DRUG LABEL
Date: 20241101

ACTIVE INGREDIENTS: ALCOHOL 65 mL/100 mL
INACTIVE INGREDIENTS: PROPYLENE GLYCOL; CARBOMER INTERPOLYMER TYPE A (55000 CPS); ALOE VERA LEAF; MALTODEXTRIN; WATER; GLYCERIN; AMINOMETHYL PROPANEDIOL

Active Ingredient

Alcohol Denat 70%

Purpose

Antiseptic

Indications and Usage

For handwashing to decrease bacteria on the skin. Recommended for repeated use.

Warnings

Flammable, keep away from fire or flame. For external use only. Do not use in eyes. In case of eye contact flush thoroughly with water and seek medical attention. Stop use and ask doctor if irritation adn redness develop and persists for more than 72 hours.

Keep out of reach of children. If swallowed, get medical help or contact a Poison Control Center right away.

Dosage and Administration

Dispense an adequate amount in your palm to cover all surfaces of hands completely. Rub hands together until dry. Does not require rinsing.

Inactive Ingredients

Water, Aloe Barbadensis Leaf Juice, Maltodextrin, Glycerin, Propylene Glycol, Fragrance, Acrylates/C10-30 Alkyl Acrylate Crosspolymer, Aminomethyl propanol.